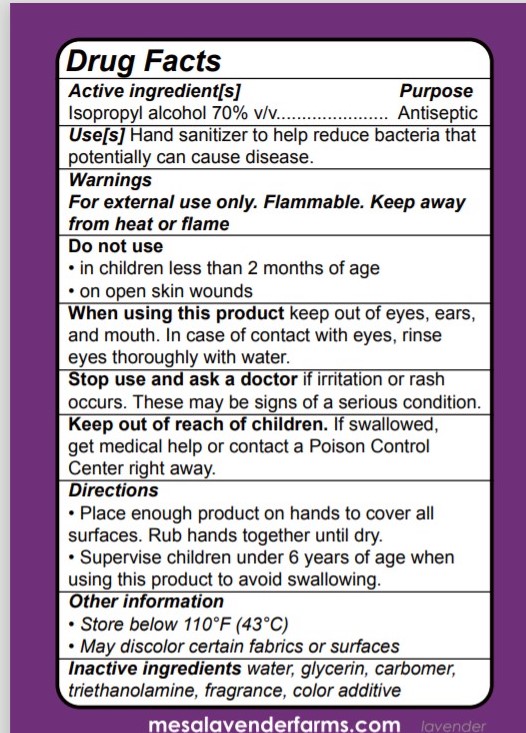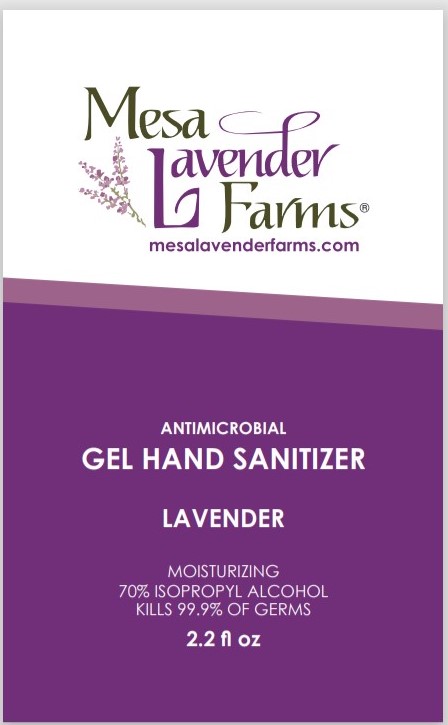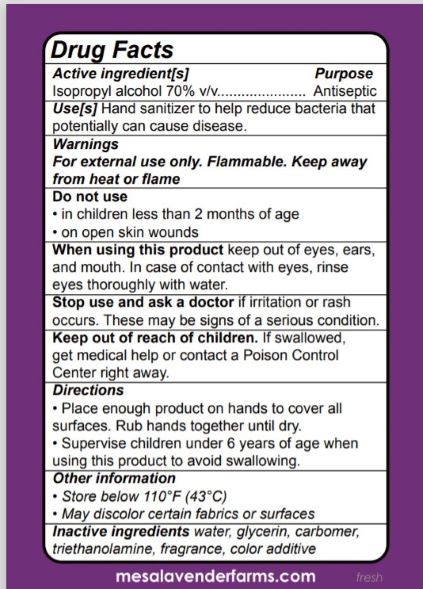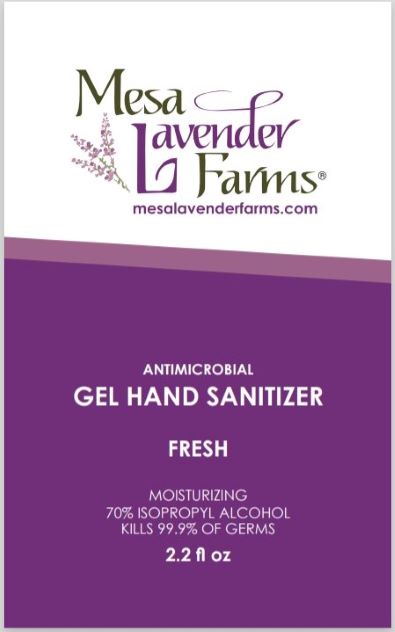 DRUG LABEL: Hand Sanitizer
NDC: 80311-252 | Form: GEL
Manufacturer: Mesa Lavender Farms
Category: otc | Type: HUMAN OTC DRUG LABEL
Date: 20201129

ACTIVE INGREDIENTS: ISOPROPYL ALCOHOL 0.705 mL/1 mL
INACTIVE INGREDIENTS: FD&C RED NO. 40; LINALOOL, (+/-)-; CARBOMER 940; WATER; TROLAMINE; FD&C BLUE NO. 1; GLYCERIN; NONOXYNOL-9

Gel Sanitizer

ACTIVE INGREDIENT

Isopropyl alcohol 70% v/v...................... Antiseptic

Active ingredient[s] Purpose

Isopropyl alcohol 70% v/v...................... Antiseptic

Use[s]

Hand sanitizer to help reduce bacteria that potentially can cause disease.

Warnings

For external use only. Flammable. Keep away from heat or flame

Do not use

in children less than 2 months of age

on open skin wounds

When using this product

keep out of eyes, ears, and mouth. In case of contact with eyes, rinse eyes thoroughly with water.

Stop use and ask a doctor

if irritation or rash occurs. These may be signs of a serious condition.

Keep out of reach of children. If swallowed, get medical help or contact a Poison Control Center right away.

Directions

Place enough product on hands to cover all surfaces. Rub hands together until dry.

Supervise children under 6 years of age when using this product to avoid swallowing.

Other Information

Store below 110°F (43°C)

May discolor certain fabrics or surfaces

Inactive ingredients

water, glycerin, carbomer, triethanolamine, fragrance, color additive

PACKAGE LABEL

66 ml NDC: 80311-252-21

66 ml NDC: 80311-000-21